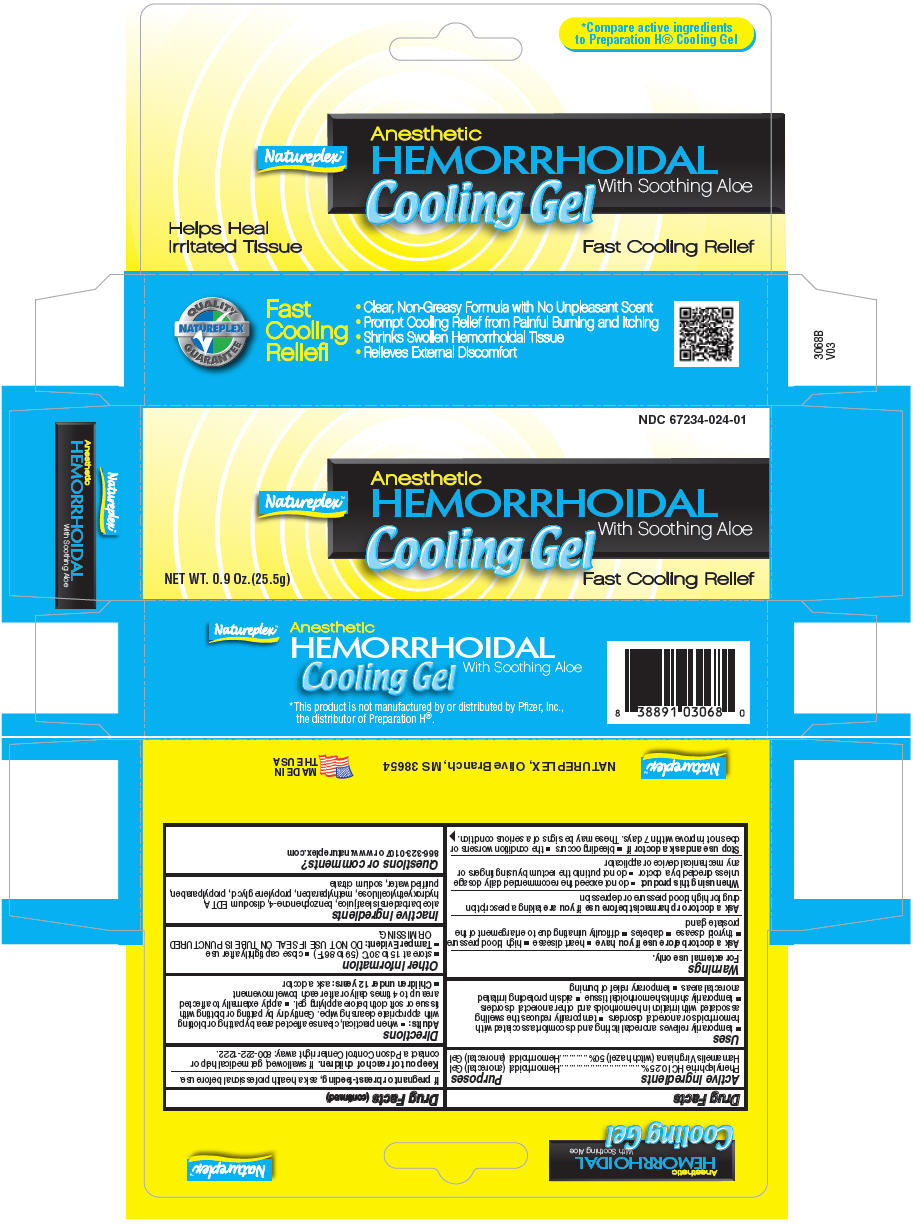 DRUG LABEL: Natureplex 
NDC: 67234-024 | Form: GEL
Manufacturer: Natureplex LLC
Category: otc | Type: HUMAN OTC DRUG LABEL
Date: 20241231

ACTIVE INGREDIENTS: WITCH HAZEL 0.5 mg/1 g; PHENYLEPHRINE HYDROCHLORIDE 0.0025 mg/1 g
INACTIVE INGREDIENTS: ANHYDROUS TRISODIUM CITRATE; ALOE VERA LEAF; BENZOPHENONE; HYDROXYETHYL CELLULOSE (280 MPA.S AT 2%); EDETATE DISODIUM; METHYLPARABEN; PROPYLENE GLYCOL; PROPYLPARABEN; WATER

Natureplex™
Hemorrhoidal Cooling Gel

Drug Facts

ACTIVE INGREDIENT

PURPOSE

Active ingredients | Purposes
Phenylephrine HCl 0.25% | Hemorrhoidal (anorectal) Gel
Hamamelis Virginiana (witch hazel) 50% | Hemorrhoidal (anorectal) Gel

Uses

- temporarily relieves anorectal itching and discomfort associated with hemorrhoids or anorectal disorders
- temporarily reduces the swelling associated with irriation in hemorrhoids and other anorectal disorders
- temporarily shrinks hemorrhoidal tissue
- aids in protecting irritated anorectal areas
- temporary relief of burning

Warnings

For external use only.

Ask a doctor before use if you have

- heart disease
- high blood pressure
- thyroid disease
- diabetes
- difficulty urinating due to enlargement of the prostate gland

Ask a doctor or pharmacist before use if you are taking a prescription drug for high blood pressure or depression

When using this product

- do not exceed the recommended daily dosage unless directed by a doctor
- do not put into the rectum by using fingers or any mechanical device or applicator

Stop use and ask a doctor if

- bleeding occurs
- the condition worsens or does not improve within 7 days. These may be signs of a serious condition.

PREGNANCY OR BREAST FEEDING

If pregnant or breast-feeding, ask a health professional before use.

Keep out of reach of children. If swallowed, get medical help or contact a Poison Control Center right away: 800-222-1222.

Directions

Adults:

- when practical, cleanse affected area by patting or blotting with appropriate cleansing wipe. Gently dry by patting or blotting with tissue or soft cloth before applying gel.
- apply externally to affected area up to 4 times daily or after each bowel movement
- Children under 12 years: ask a doctor

Other information

- store at 15 to 30°C (59 to 86°F)
- close cap tightly after use
- Tamper Evident: DO NOT USE IF SEAL ON TUBE IS PUNCTURED OR MISSING.

Inactive ingredients

aloe barbadensis leaf juice, benzophenone-4, disodium EDTA, hydroxyethylcellulose, methylparaben, propylene glycol, propylparaben, purified water, sodium citrate

Questions or comments?

866-323-0107 or www.natureplex.com

PRINCIPAL DISPLAY PANEL - 25.5 g Tube Box

NDC 67234-024-01

Natureplex™

Anesthetic
HEMORRHOIDAL
Cooling Gel With Soothing Aloe

NET WT. 0.9 Oz.(25.5g)

Fast Cooling Relief